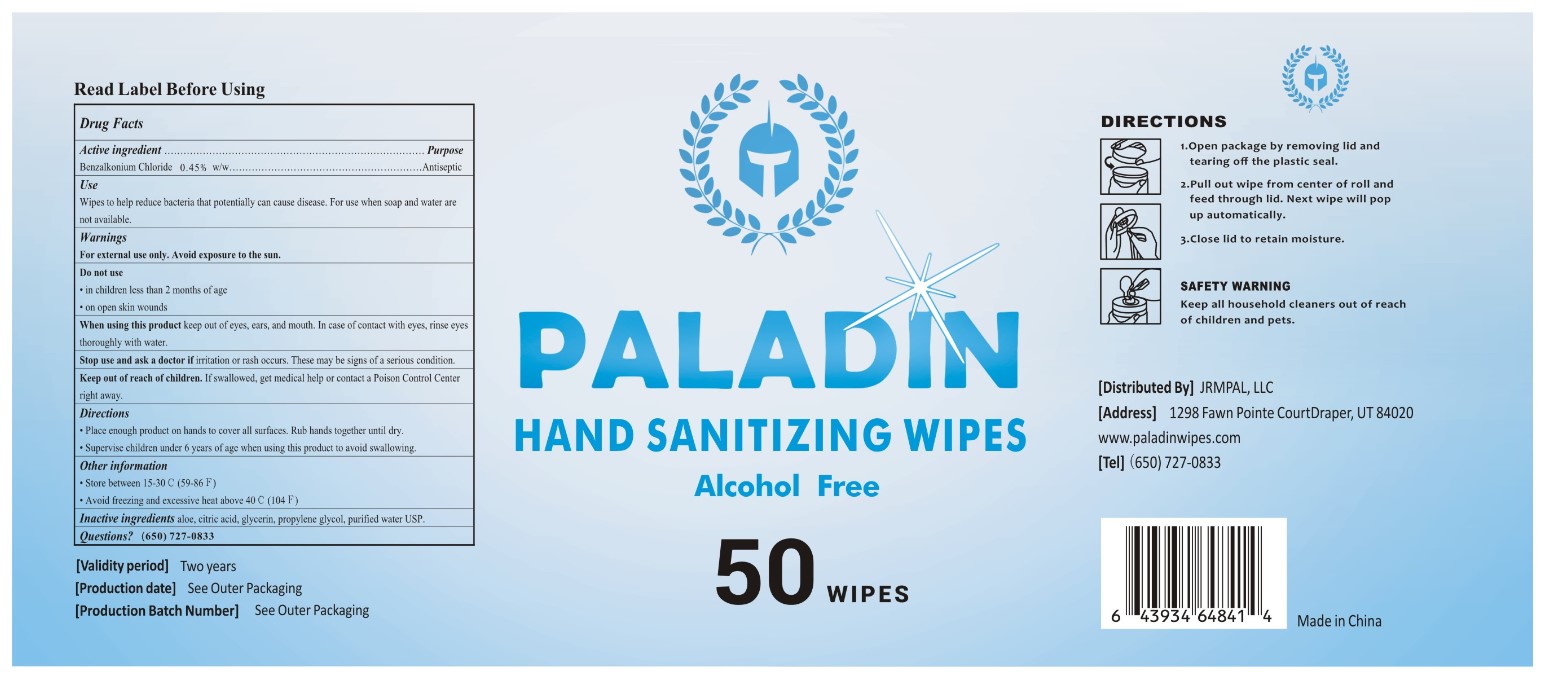 DRUG LABEL: HAND SANITIZING WIPES
NDC: 79621-529 | Form: CLOTH
Manufacturer: Tianjin Zejun Int'l Trade Co., Ltd
Category: otc | Type: HUMAN OTC DRUG LABEL
Date: 20220113

ACTIVE INGREDIENTS: BENZALKONIUM CHLORIDE 0.45 g/100 g
INACTIVE INGREDIENTS: ALOE 0.05 g/100 g; ANHYDROUS CITRIC ACID 0.01 g/100 g; GLYCERIN 0.5 g/100 g; PROPYLENE GLYCOL 0.3 g/100 g; WATER 98.69 g/100 g

Active Ingredient(s)

Benzalkonium Chloride 0.45% w/w. Purpose: Antiseptic

Purpose

Antiseptic, Hand Sanitizer

Use

Wipes to help reduce bacteria that potentially can cause disease. For use when soap and water are not available.

Warnings

For external use only. Flammable. Avoid exposure to the sun.

Do not use

- in children less than 2 months of age
- on open skin wounds

When using this product keep out of eyes, ears, and mouth. In case of contact with eyes, rinse eyes thoroughly with water.
Stop use and ask a doctor if irritation or rash occurs. These may be signs of a serious condition.
Keep out of reach of children. If swallowed, get medical help or contact a Poison Control Center right away.

Stop use and ask a doctor if irritation or rash occurs. These may be signs of a serious condition.

Keep out of reach of children. If swallowed, get medical help or contact a Poison Control Center right away.

Directions

- Place enough product on hands to cover all surfaces. Rub hands together until dry.
- Supervise children under 6 years of age when using this product to avoid swallowing.

Other information

- Store between 15-30C (59-86F)
- Avoid freezing and excessive heat above 40C (104F)

Inactive ingredients

aloe, citric acid, glycerin, propylene glycol, purified water USP.

Package Label - Principal Display Panel

50 Wipes in 1 Pail NDC: 79621-529-01